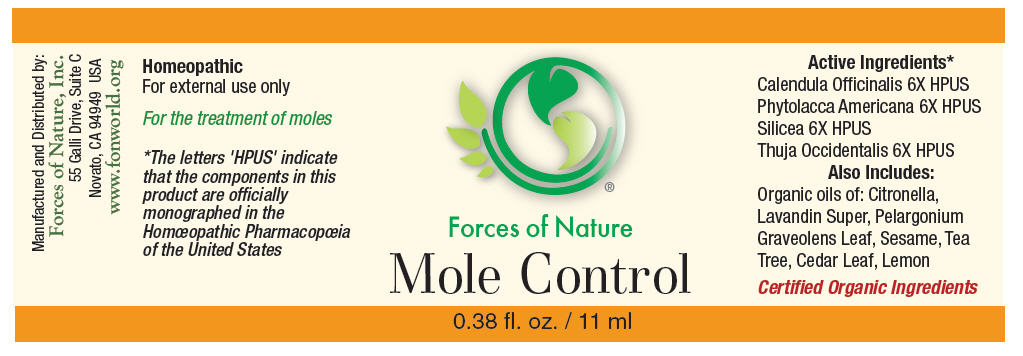 DRUG LABEL: Nevi (Mole) Control
NDC: 51393-6666 | Form: SOLUTION/ DROPS
Manufacturer: Forces of Nature
Category: homeopathic | Type: HUMAN OTC DRUG LABEL
Date: 20100824

ACTIVE INGREDIENTS: CALENDULA OFFICINALIS FLOWERING TOP 6 [hp_X]/1000 mL; PHYTOLACCA AMERICANA ROOT 6 [hp_X]/1000 mL; SILICON DIOXIDE 6 [hp_X]/1000 mL; THUJA OCCIDENTALIS LEAFY TWIG 6 [hp_X]/1000 mL

Mole Control

Drug Facts

Indications

For the treatment of moles.

ACTIVE INGREDIENT

PURPOSE

Homeopathic Active Ingredients [The letters 'HPUS' indicate that the components in this product are officially monographed in the Homœopathic Pharmacopœia of the United States.]
Equal parts of: | Purpose
Calendula Officinalis 6X HPUS | Promotes healthy skin and healing
Phytolacca Americana 6X HPUS | Remedy for skin tags, moles and warts
Silicea 6X HPUS | Remedy for boils and pustules, unhealthy skin
Thuja occidentalis 6X HPUS | Remedy for moles and nevi

Inactive Ingredients

Citronella Oil, Lavandin Super Oil, Pelargonium Graveolens Leaf Oil, Sesame Oil, Tea Tree Oil, Thuja Oil, Lemon Oil.

Directions

Apply directly to mole(s) and rub gently into skin. Wash hands with warm water and soap before and after treatment. Mole Control can be used to remove moles occurring anywhere on the body. If it is applied to facial moles, avoid contact with the eyes. Apply it three times a day.

Warnings

WHEN USING

Some individuals may be sensitive to essential oils. Begin with a small drop to determine if the product causes any increased redness or irritation and discontinue use if it irritates your skin.

PREGNANCY OR BREAST FEEDING

AS with all medicine, if you are pregnant or breast-feeding, ask a health professional before use.

KEEP OUT OF REACH OF CHILDREN

Keep out of the reach of children. If accidental ingestion of more than several drops occurs, get medical help or contact a Poison Control Center.

For external use only. Do not apply to the eyes or mucous membranes. Keep all medicines out of the reach of children.

Stop use and ask a doctor if condition worsens or symptoms become worse after more than 7 days of treatment.

Manufactured by:
Forces of Nature, Inc.
55 Galli Drive, Suite C
Novato, CA 94949 USA
www.fonworld.org

Product questions?

877-975-3797

NDC #: 51393-6666-1 (11ml) // 51393-6666-2 (33ml)

PRINCIPAL DISPLAY PANEL - 11 ml Bottle Label

Forces of Nature

Mole Control

0.38 fl. oz. / 11 ml